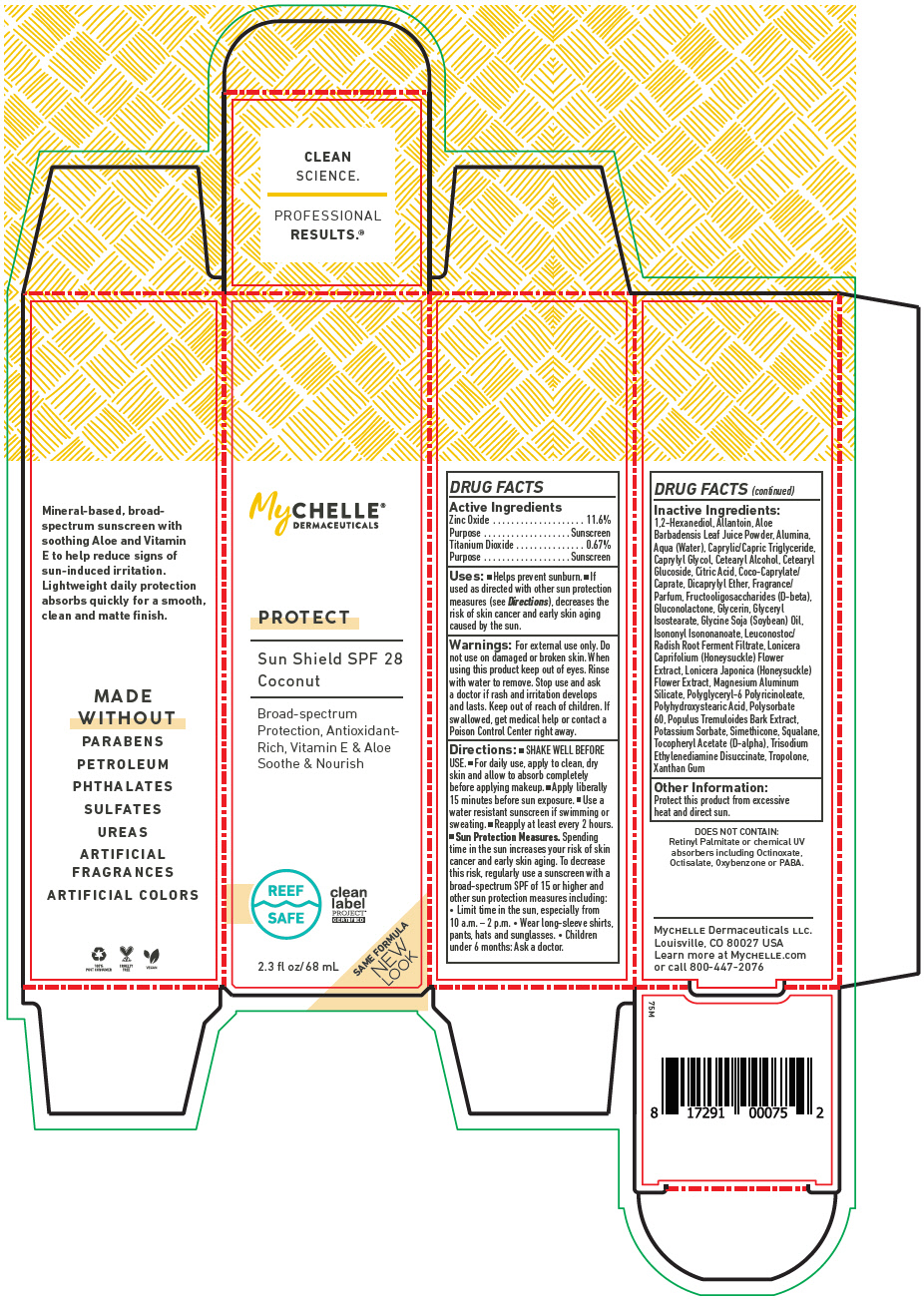 DRUG LABEL: MyChelle Dermaceuticals Sun Shield SPF 28 Coconut 
NDC: 72805-051 | Form: LOTION
Manufacturer: French Transit, Ltd.
Category: otc | Type: HUMAN OTC DRUG LABEL
Date: 20220106

ACTIVE INGREDIENTS: Zinc Oxide 11.6 g/100 mL; Titanium Dioxide 0.67 g/100 mL
INACTIVE INGREDIENTS: WATER; 1,2-Hexanediol; Allantoin; ALOE VERA LEAF; ALUMINUM OXIDE; MEDIUM-CHAIN TRIGLYCERIDES; Caprylyl Glycol; CETOSTEARYL ALCOHOL; Cetearyl Glucoside; ANHYDROUS CITRIC ACID; COCOYL CAPRYLOCAPRATE; Dicaprylyl Ether; Dimethicone; Gluconolactone; Glycerin; Glyceryl Isostearate; SOYBEAN OIL; Isononyl Isononanoate; Leuconostoc/Radish Root Ferment Filtrate; LONICERA CAPRIFOLIUM FLOWER; LONICERA JAPONICA FLOWER; Magnesium Aluminum Silicate; POLYHYDROXYSTEARIC ACID (2300 MW); Polysorbate 60; POPULUS TREMULOIDES BARK; Potassium Sorbate; Silicon Dioxide; Squalane; .ALPHA.-TOCOPHEROL ACETATE, D-; Trisodium Ethylenediamine Disuccinate; Tropolone; Xanthan Gum

MyChelle® Dermaceuticals Sun Shield SPF 28 Coconut
Protect

DRUG FACTS

Active Ingredients

PURPOSE

Zinc Oxide | 11.6%
Purpose | Sunscreen
Titanium Dioxide | 0.67%
Purpose | Sunscreen

Uses

- Helps prevent sunburn.
- If used as directed with other sun protection measures (see Directions), decreases the risk of skin cancer and early skin aging caused by the sun.

Warnings

For external use only. Do not use on damaged or broken skin. When using this product keep out of eyes. Rinse with water to remove. Stop use and ask a doctor if rash and irritation develops and lasts.

Keep out of reach of children. If swallowed, get medical help or contact a Poison Control Center right away.

Directions

- SHAKE WELL BEFORE USE.
- For daily use, apply to clean, dry skin and allow to absorb completely before applying makeup.
- Apply liberally 15 minutes before sun exposure.
- Use a water resistant sunscreen if swimming or sweating.
- Reapply at least every 2 hours.
- Sun Protection Measures. Spending time in the sun increases your risk of skin cancer and early skin aging. To decrease this risk, regularly use a sunscreen with a broad-spectrum SPF of 15 or higher and other sun protection measures including:
  - Limit time in the sun, especially from 10 a.m. – 2 p.m.
  - Wear long-sleeve shirts, pants, hats and sunglasses.
  - Children under 6 months: Ask a doctor.

Inactive Ingredients

1,2-Hexanediol, Allantoin, Aloe Barbadensis Leaf Juice Powder, Alumina, Aqua (Water), Caprylic/Capric Triglyceride, Caprylyl Glycol, Cetearyl Alcohol, Cetearyl Glucoside, Citric Acid, Coco-Caprylate/Caprate, Dicaprylyl Ether, Fragrance/Parfum, Fructooligosaccharides (D-beta), Gluconolactone, Glycerin, Glyceryl Isostearate, Glycine Soja (Soybean) Oil, Isononyl Isononanoate, Leuconostoc/Radish Root Ferment Filtrate, Lonicera Caprifolium (Honeysuckle) Flower Extract, Lonicera Japonica (Honeysuckle) Flower Extract, Magnesium Aluminum Silicate, Polyglyceryl-6 Polyricinoleate, Polyhydroxystearic Acid, Polysorbate 60, Populus Tremuloides Bark Extract, Potassium Sorbate, Simethicone, Squalane, Tocopheryl Acetate (D-alpha), Trisodium Ethylenediamine Disuccinate, Tropolone, Xanthan Gum

Other Information

Protect this product from excessive heat and direct sun.

PRINCIPAL DISPLAY PANEL - 68 mL Tube Box

MyCHELLE®
DERMACEUTICALS

PROTECT

Sun Shield SPF 28
Coconut

Broad-spectrum
Protection, Antioxidant-
Rich, Vitamin E & Aloe
Soothe & Nourish

REEF
SAFE

clean
label
PROJECT®
CERTIFIED

2.3 fl oz/68 mL

SAME FORMULA
NEW
LOOK